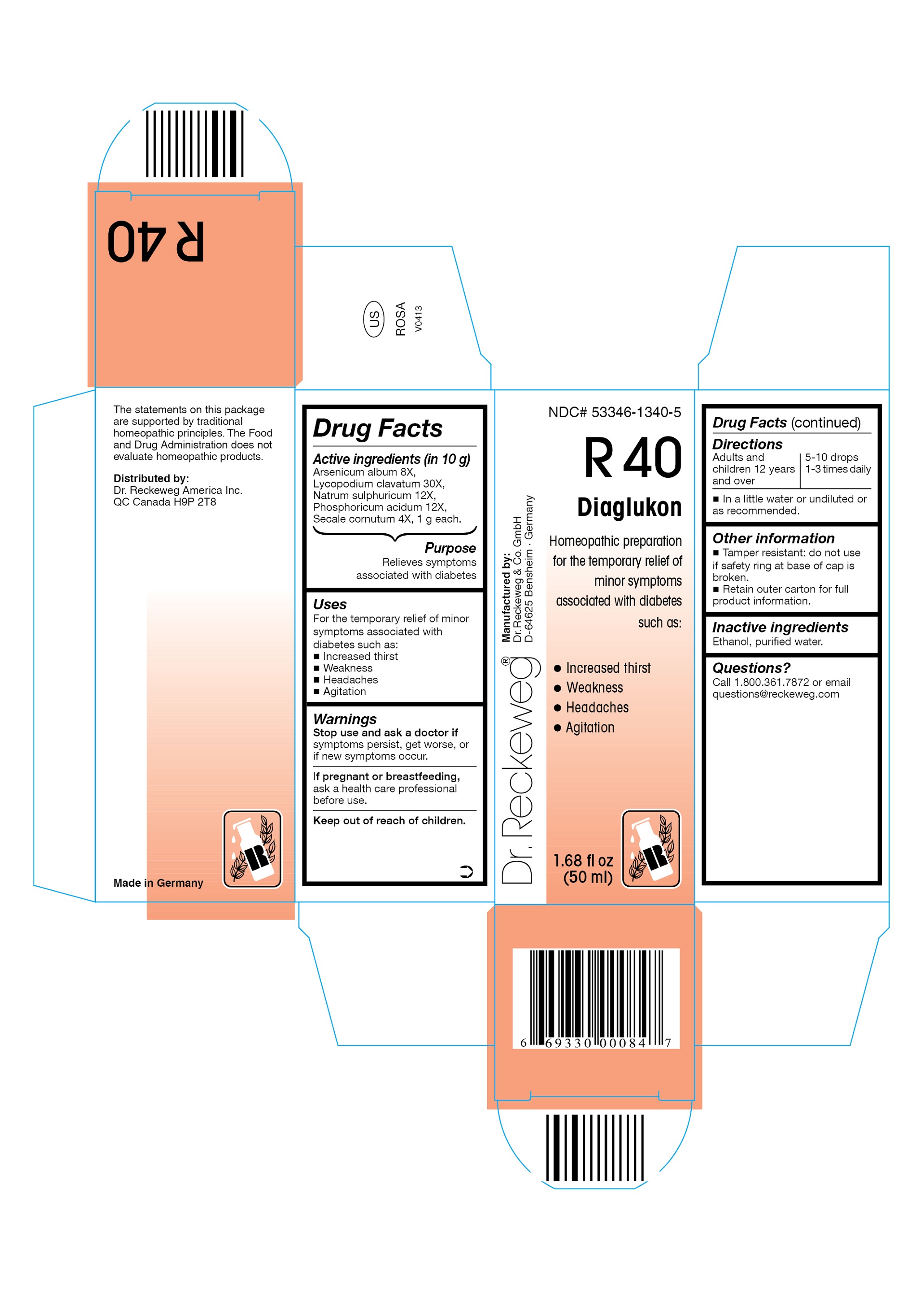 DRUG LABEL: DR. RECKEWEG R40 Diaglukon
NDC: 53346-1340 | Form: LIQUID
Manufacturer: PHARMAZEUTISCHE FABRIK DR. RECKEWEG & CO
Category: homeopathic | Type: HUMAN OTC DRUG LABEL
Date: 20130405

ACTIVE INGREDIENTS: ARSENIC TRIOXIDE 8 [hp_X]/50 mL; LYCOPODIUM CLAVATUM SPORE 30 [hp_X]/50 mL; SODIUM SULFATE 12 [hp_X]/50 mL; PHOSPHORIC ACID 12 [hp_X]/50 mL; CLAVICEPS PURPUREA SCLEROTIUM 4 [hp_X]/50 mL
INACTIVE INGREDIENTS: ALCOHOL; WATER

DR. RECKEWEG R40 Diaglukon

Active ingredients

Arsenicum album 8X, Lycopodium clavatum 30X, Natrum sulphuricum 12X, Phosphoricum acidum 12X, Secale cornutum 4X, 1 g each in 10 g.

Purpose

Relieves symptoms associated with diabetes

Uses

For the temporary relief of minor symptoms associated with diabetes such as:

- Increased thirst
- Weakness
- Headaches
- Agitation

Warnings

Stop use and ask a doctor if symptoms persist, get worse, or if new symptoms occur.

PREGNANCY OR BREAST FEEDING

If pregnant or breastfeeding, ask a health care professional before use.

Keep out of reach of children.

Directions

Adults and children ≥ 12 years 5-10 drops 1-3 times daily in a little water or undiluted or as recommended.

Other information

- Tamper resistant: do not use if safety ring at base of cap is broken.
- Retain outer carton for full product information.

Inactive ingredients

Ethanol, purified water.

Questions?

Call 1-800-361-7872 or email questions@reckeweg.com

PACKAGE LABEL

NDC# 53346-1340-5

Dr. Reckeweg R40 Diaglukon

Homeopathic preparation for the temporary relief of minor symptoms associated with diabetes such as:

- Increased thirst

- Weakness

- Headaches

- Agitation

Manufactured by:

Dr. Reckeweg Co. GmbH

D-64625 Bensheim

Germany

1.68 fl oz
(50 ml)